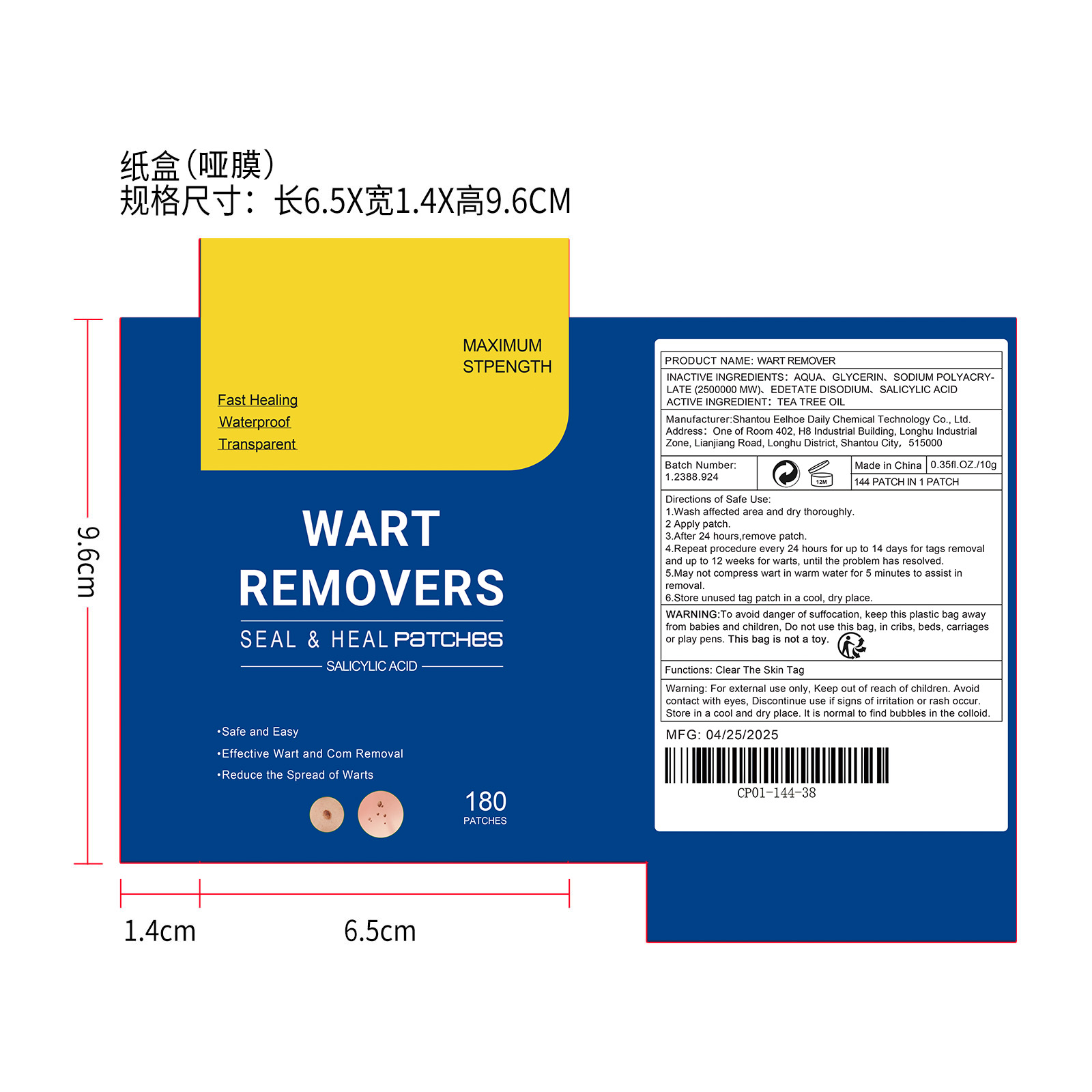 DRUG LABEL: WART REMOVER
NDC: 85064-014 | Form: PATCH
Manufacturer: Shantou Eelhoe Daily Chemical Technology Co., Ltd.
Category: otc | Type: HUMAN OTC DRUG LABEL
Date: 20251127

ACTIVE INGREDIENTS: TEA TREE OIL 0.9 mg/180 mg
INACTIVE INGREDIENTS: EDETATE DISODIUM 0.18 mg/180 mg; AQUA 162.54 mg/180 mg; SALICYLIC ACID 0.9 mg/180 mg; GLYCERIN 14.4 mg/180 mg; SODIUM POLYACRYLATE (2500000 MW) 1.08 mg/180 mg

ACTIVE INGREDIENT

TEA TREE OIL

PURPOSE

Clear The Skin Tag

WHEN USING

1.Wash affected area and dry thoroughly.
2 Apply patch.
3.After 24 hours,remove patch.
4.Repeat procedure every 24 hours for up to 14 days for tags removal and up to 12 weeks for warts, until the problem has resolved.
5.May not compress wart in warm water for 5 minutes to assist in removal.
6.Store unused tag patch in a cool, dry place.

WARNINGS

For external use only, Keep out of reach of children. Avoid contact with eyes, Discontinue use if signs of irritation or rash occur. Store in a cool and dry place. It is normal to find bubbles in the colloid.

DO NOT USE

Discontinue use if signs of irritation or rash occur.

STOP USE

Discontinue use if signs of irritation or rash occur.

KEEP OUT OF REACH OF CHILDREN

For external use only, Keep out of reach of children.

STORAGE AND HANDLING

Store in a cool and dry place.

INACTIVE INGREDIENT

AQUA、GLYCERIN、SODIUM POLYACRYLATE (2500000 MW)、EDETATE DISODIUM、SALICYLIC ACID

DOSAGE AND ADMINISTRATION

1.Wash affected area and dry thoroughly. 2 Apply patch. 3.After 24 hours,remove patch. 4.Repeat procedure every 24 hours for up to 14 days for tags removal and up to 12 weeks for warts, until the problem has resolved, 5.May not compress wart in warm water for 5 minutes to assist in removal. 6.Store unused tag patch in a cool, dry place.

INDICATIONS AND USAGE

1.Wash affected area and dry thoroughly. 2 Apply patch. 3.After 24 hours,remove patch. 4.Repeat procedure every 24 hours for up to 14 days for tags removal and up to 12 weeks for warts, until the problem has resolved, 5.May not compress wart in warm water for 5 minutes to assist in removal. 6.Store unused tag patch in a cool, dry place.